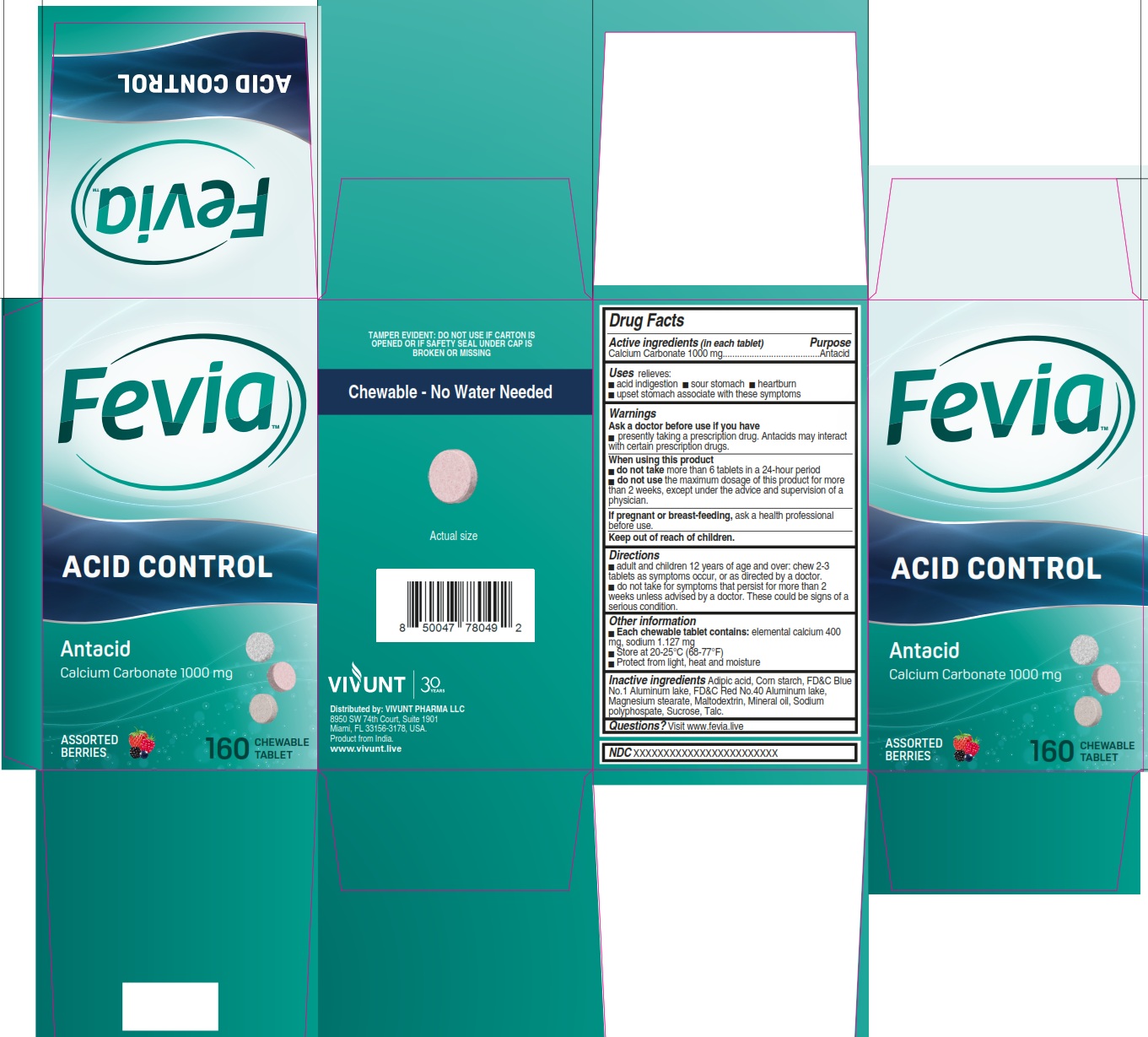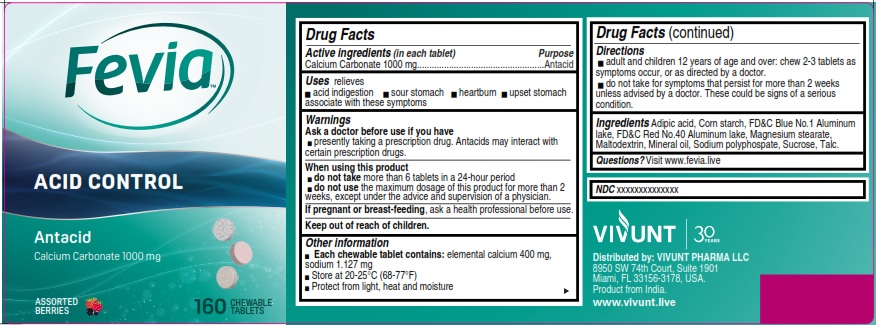 DRUG LABEL: FEVIA Acid Control
NDC: 82706-027 | Form: TABLET, CHEWABLE
Manufacturer: VIVUNT PHARMA LLC
Category: otc | Type: HUMAN OTC DRUG LABEL
Date: 20260226

ACTIVE INGREDIENTS: CALCIUM CARBONATE 1000 mg/1 1
INACTIVE INGREDIENTS: FD&C BLUE NO. 1 ALUMINUM LAKE; FD&C RED NO. 40 ALUMINUM LAKE; MAGNESIUM STEARATE; MALTODEXTRIN; STARCH, CORN; SODIUM POLYMETAPHOSPHATE; SUCROSE; ADIPIC ACID; TALC; MINERAL OIL

FEVIA Acid Control 160

Drug Facts

Active ingredients (in each tablet)

Calcium Carbonate 1000 mg

Purpose

- Antacid

Uses

relieves:

- acid indigestion
- sour stomach
- heartburn
- upset stomach associate with these symptoms

Warnings

Ask a doctor before use if you have

- presently taking a prescription drug. Antacids may interact with certain prescription drugs.

When using this product

- do not takemore than 6 tablets in a 24 - hour period

do not use

- the maximum dosage of this product for more than 2 weeks, except under the advice and supervision of a physician

If pregnant or breast-feeding,

ask a health professional before use.

Keep out of reach of children.

Directions

- adult and children 12 years of age and over: chew 2-3 tablets as symptoms occur, or as directed by a doctor.
- do not take for symptoms that persist for more than 2 weeks unless advised by a doctor. These could be signs of a serious condition.

Other information

- Each chewable tabet contains:elemental calcium 400 mg, sodium 1.127 mg
- Store at 20-25°C (68-77°F)
- Protect from light, heat and moisture

Inactive ingredients

Adipic acid, Assorted berries flavor, Corn starch, Magnesium stearate, Maltodextrin, Mineral oil, Sodium polyphospate, Sucrose, Talc.

Questions?

Visit www.fevia.live

Distributed by

VIVUNT

Distributed by: VIVUNT PHARMA LLC

8950 SW 74th Court, Suite 1901

Miami, FL 33156-3178, USA.

Product from India.

www.vivunt.live

Pakage PDP

FEVIA™

ACID CONTROL

Antacid

Calcium Carbonate 1000 mg

ASSORTED BERRIES

160 CHEWABLE TABLET

TAMPER EVIDENT: DO NOT USE IF CARTON IS OPEN OR IF SAFETY SEAL UNDER CAP IS BROKEN OR MISSING

Chewable - No Water Needed

Actual size